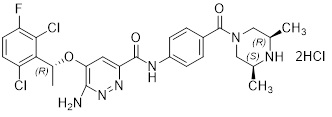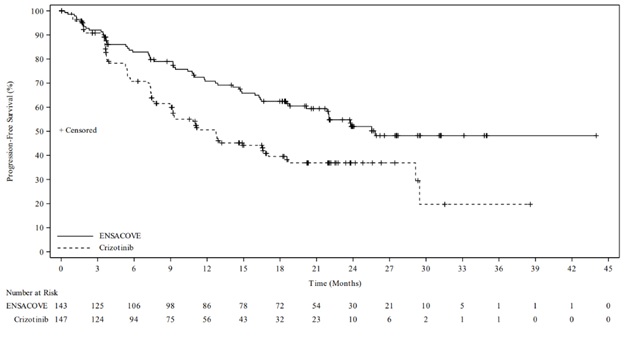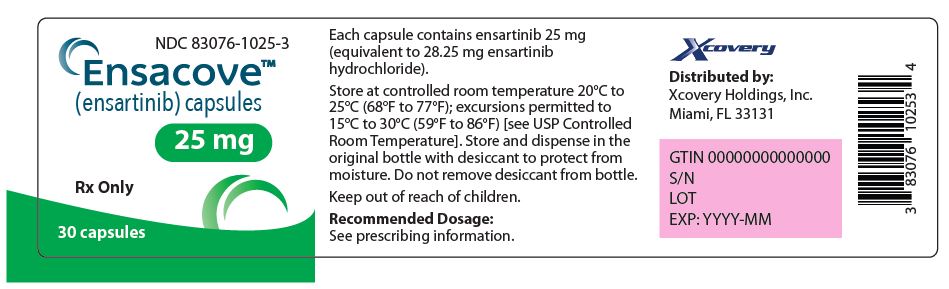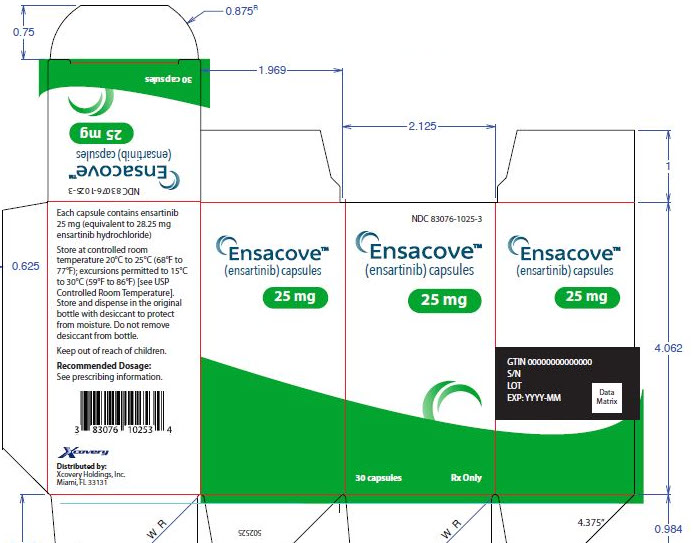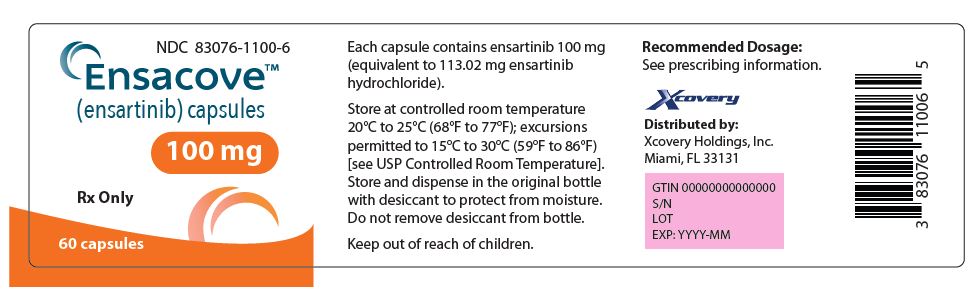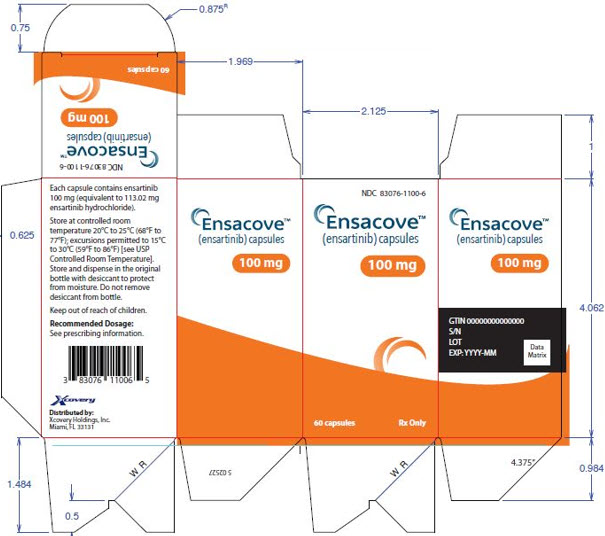 DRUG LABEL: ENSACOVE
NDC: 83076-1025 | Form: CAPSULE
Manufacturer: Xcovery Holdings, Inc.
Category: prescription | Type: HUMAN PRESCRIPTION DRUG LABEL
Date: 20260217

ACTIVE INGREDIENTS: ENSARTINIB HYDROCHLORIDE 25 mg/1 1
INACTIVE INGREDIENTS: HYPROMELLOSE, UNSPECIFIED; TITANIUM DIOXIDE; MICROCRYSTALLINE CELLULOSE; STEARIC ACID; SHELLAC; ISOPROPYL ALCOHOL; DEHYDRATED ALCOHOL; BUTYL ALCOHOL; PROPYLENE GLYCOL; FD&C BLUE NO. 2; AMMONIA

HIGHLIGHTS OF PRESCRIBING INFORMATION

These highlights do not include all the information needed to use ENSACOVE safely and effectively. See full prescribing information for ENSACOVE.
ENSACOVETM (ensartinib) capsules, for oral use
Initial U.S. Approval: 2024

1 INDICATIONS AND USAGE

ENSACOVE is a kinase inhibitor indicated for the treatment of adult patients with anaplastic lymphoma kinase (ALK)-positive locally advanced or metastatic non-small cell lung cancer (NSCLC) as detected by an FDA-approved test who have not previously received an ALK-inhibitor. (1, 2.1)

2 DOSAGE AND ADMINISTRATION

- Select patients with ALK-positive locally advanced or metastatic NSCLC for treatment with ENSACOVE. (2.1)
- Prior to initiating ENSACOVE, evaluate liver function tests and fasting blood glucose. (2.2)
- Recommended dosage: 225 mg orally once daily with or without food until disease progression or unacceptable toxicity. (2.3)

3 DOSAGE FORMS AND STRENGTHS

Capsules: 25 mg and 100 mg of ensartinib (3)

4 CONTRAINDICATIONS

Hypersensitivity reaction to ENSACOVE, FD&C Yellow No. 5 (tartrazine), or to any of its components. (4)

5 WARNINGS AND PRECAUTIONS

- Interstitial Lung Disease (ILD)/Pneumonitis: Monitor patients for new or worsening symptoms indicative of ILD/pneumonitis. Permanently discontinue in patients with ILD/pneumonitis. (5.1)
- Hepatotoxicity: Monitor liver function tests during treatment with ENSACOVE. Withhold, reduce the dose, or permanently discontinue ENSACOVE based on severity. (5.2)
- Dermatologic Adverse Reaction: Monitor for dermatologic adverse reactions during treatment with ENSACOVE. Withhold, reduce the dose, or permanently discontinue ENSACOVE based on severity. (5.3)
- Bradycardia: Monitor heart rate regularly during treatment with ENSACOVE. Withhold, reduce the dose, or permanently discontinue ENSACOVE based on severity. (5.4)
- Hyperglycemia: Monitor serum glucose periodically during treatment with ENSACOVE. Withhold, reduce the dose, or permanently discontinue ENSACOVE based on severity. (5.5)
- Visual Disturbances: Advise patients to report visual symptoms during treatment with ENSACOVE. Withhold ENSACOVE and obtain ophthalmologic evaluation, then reduce the dose or permanently discontinue ENSACOVE. (5.6)
- Increased Creatine Phosphokinase (CPK): Monitor CPK periodically during treatment with ENSACOVE. Withhold, reduce the dose, or permanently discontinue ENSACOVE based on severity. (5.7)
- Hyperuricemia: Monitor uric acid periodically during treatment with ENSACOVE. Withhold, reduce the dose, or permanently discontinue ENSACOVE based on severity. (5.8)
- Embryo-Fetal Toxicity: Can cause fetal harm. Advise patients of the potential risk to a fetus and to use effective contraception. (5.9)

6 ADVERSE REACTIONS

- Most common adverse reactions (incidence ≥20%) were rash, musculoskeletal pain, constipation, pruritus, cough, nausea, edema, vomiting, fatigue, and pyrexia. (6.1)
- Most common Grade 3-4 laboratory abnormality (incidence ≥2%) were increased uric acid, decreased lymphocytes, increased alanine aminotransferase, decreased phosphate, increased gamma glutamyl transferase, increased magnesium, increased amylase, decreased sodium, increased glucose, decreased hemoglobin, increased bilirubin, decreased potassium, and increased creatine phosphokinase. (6.1)

To report SUSPECTED ADVERSE REACTIONS, contact Xcovery Holdings, Inc. at (866) 367-2268 or FDA at 1-800-FDA-1088 or www.fda.gov/medwatch.

7 DRUG INTERACTIONS

- Moderate or Strong CYP3A Inhibitors: Avoid concomitant use with ENSACOVE. (7.1)
- Moderate or Strong CYP3A Inducers: Avoid concomitant use with ENSACOVE. (7.1)
- P-gp Inhibitor: Avoid concomitant use with ENSACOVE. (7.1)

8 USE IN SPECIFIC POPULATIONS

- Lactation: Advise not to breastfeed. (8.2)
- Severe Hepatic Impairment: Avoid use of ENSACOVE in patients with severe hepatic impairment. (8.6)

FULL PRESCRIBING INFORMATION

1 INDICATIONS AND USAGE

ENSACOVE is indicated for the treatment of adult patients with anaplastic lymphoma kinase (ALK)-positive locally advanced or metastatic non-small cell lung cancer (NSCLC)as detected by an FDA-approved test [see Dosage and Administration (2.1)] who have not previously received an ALK-inhibitor.

2 DOSAGE AND ADMINISTRATION

2.1 Patient Selection

Select patients for the treatment of locally advanced or metastatic NSCLC with ENSACOVE based on the presence of ALK rearrangement(s) in tumor specimens [see Clinical Studies (14.1)].

Information on FDA-approved tests for the detection of ALK rearrangements in NSCLC is available at http://www.fda.gov/CompanionDiagnostics.

2.2 Recommended Testing and Advice Prior to Initiating ENSACOVE

Prior to initiating ENSACOVE, evaluate liver function tests [see Warnings and Precautions (5.2)] and fasting blood glucose [see Warnings and Precautions (5.5)].

2.3 Recommended Dosage

The recommended dosage of ENSACOVE is 225 mg orally once daily, with or without food [see Clinical Pharmacology (12.3)], until disease progression or unacceptable toxicity.

Swallow capsules whole, do not crush or chew. Do not open or dissolve the contents of the capsule. Take ENSACOVE at the same time each day.

Missed dose

If a dose is missed, then take the missed dose as soon as possible unless the next dose is due within 12 hours. Do not take 2 doses on the same day.

Vomiting

If vomiting occurs after taking a dose, do not take an additional dose and take the next dose at its scheduled time.

2.4 Dosage Modification for Adverse Reactions

The recommended dose reductions for adverse reactions are provided in Table 1.

Table 1: Recommended Dose Reductions for Adverse Reactions
Dose Reduction | Recommended Dose and Schedule
First | 200 mg orally once daily
Second | 150 mg orally once daily
Permanently discontinue ENSACOVE if patients are unable to tolerate 150 mg orally once daily.

Once the dose has been reduced for adverse reactions, do not subsequently increase the dose of ENSACOVE.

The recommended dosage modifications for the management of adverse reactions are provided in Table 2.

Table 2: Recommended ENSACOVE Dosage Modifications for Adverse Reactions
Adverse Reaction | Severity* | ENSACOVE Dose Modification and Management for Adverse Reactions
Interstitial Lung Disease (ILD)/Pneumonitis [see Warnings and Precautions (5.1)] | Any Grade | Permanently discontinue ENSACOVE.
Hepatotoxicity [see Warnings and Precautions (5.2)] | Grade 3 or 4 elevation (greater than 5 times ULN) of either ALT or AST with concurrent total bilirubin less than or equal to 2 times ULN | - Withhold ENSACOVE until recovery to Grade ≤1 (≤3 times ULN) or to baseline. - Resume ENSACOVE at reduced dose as per Table 1.
Hepatotoxicity [see Warnings and Precautions (5.2)] | Grade 2 to 4 elevation (greater than 3 times ULN) of either ALT or AST with concurrent total bilirubin elevation greater than 2 times ULN in the absence of cholestasis or hemolysis | Permanently discontinue ENSACOVE.
Dermatologic Adverse Reactions [see Warnings and Precautions (5.3)] | Grade 1 | Consider topical corticosteroids.
Dermatologic Adverse Reactions [see Warnings and Precautions (5.3)] | Grade 2 | - Administer topical corticosteroids. - If not improved in ≤7 days after initiation of topical corticosteroids, administer oral corticosteroids. - If not improved in ≤7 days after initiation of oral corticosteroids, withhold ENSACOVE until recovery to Grade ≤1. - Resume ENSACOVE at reduced dose as per Table 1.
Dermatologic Adverse Reactions [see Warnings and Precautions (5.3)] | Grade 3 | - Withhold ENSACOVE. Administer topical corticosteroids. - If not improved after 7 days of initiation of topical corticosteroids, administer oral corticosteroids. - Resume ENSACOVE at reduced dose as per Table 1 upon improvement to Grade ≤1.
Dermatologic Adverse Reactions [see Warnings and Precautions (5.3)] | Grade 4 | - Permanently discontinue ENSACOVE. - Administer systemic corticosteroids and consider antibiotic use.
Bradycardia (HR less than 60 bpm) [see Warnings and Precautions (5.4)] | Symptomatic bradycardia | - Withhold ENSACOVE until recovery to asymptomatic bradycardia or to a resting heart rate of 60 bpm or above. - If a concomitant medication known to cause bradycardia is identified and discontinued or dose-adjusted, resume ENSACOVE at same dose upon recovery to asymptomatic bradycardia or to resting heart rate of 60 bpm or above. - If no concomitant medication known to cause bradycardia is identified, or if contributing concomitant medications are not discontinued or dose-adjusted, resume ENSACOVE at reduced dose as per Table 1 upon recovery to asymptomatic bradycardia or to resting heart rate of 60 bpm or above.
Bradycardia (HR less than 60 bpm) [see Warnings and Precautions (5.4)] | Bradycardia with life-threatening consequences, urgent intervention indicated | - Permanently discontinue ENSACOVE if no contributing concomitant medication is identified. - If contributing concomitant medication is identified and discontinued or dose- adjusted, resume ENSACOVE at reduced dose as per Table 1 upon recovery to asymptomatic bradycardia or to a resting heart rate of 60 bpm or above, with frequent monitoring as clinically indicated. - For recurrence, permanently discontinue ENSACOVE.
Hyperglycemia [see Warnings and Precautions (5.5)] | Grade 3 (greater than 250 mg/dL) despite optimal anti- hyperglycemic therapy OR Grade 4 | - Withhold ENSACOVE until hyperglycemia is adequately controlled, then resume ENSACOVE at reduced dose as per Table 1. - If adequate hyperglycemic control cannot be achieved with optimal medical management, permanently discontinue ENSACOVE.
Visual Disturbance [see Warnings and Precautions (5.6)] | Grade 2 or 3 | Withhold ENSACOVE until recovery to Grade 1 or baseline, then consider resuming at reduced dose as per Table 1.
Visual Disturbance [see Warnings and Precautions (5.6)] | Grade 4 | Permanently discontinue ENSACOVE.
Increased Creatine Phosphokinase [see Warnings and Precautions (5.7)] | CPK elevation greater than 5 times ULN | - Temporarily withhold ENSACOVE until recovery to baseline or to less than or equal to 2.5 times ULN, then resume at same dose.
Increased Creatine Phosphokinase [see Warnings and Precautions (5.7)] | CPK elevation greater than 10 times ULN or second occurrence of CPK elevation of greater than 5 times ULN | - Temporarily withhold ENSACOVE until recovery to baseline or to less than or equal to 2.5 times ULN, then resume at reduced dose as per Table 1.
Hyperuricemia [see Warnings and Precautions (5.8)] | Symptomatic or Grade 4 | - Initiate urate-lowering medication. - Withhold ENSACOVE until improvement of signs or symptoms. - Resume ENSACOVE at same or reduced dose.
Other Adverse Reactions [see Adverse Reactions (6.1)] | Grade 3 or 4 | - Withhold ENSACOVE until recovery to Grade 1 or baseline. - Resume ENSACOVE at reduced dose as per Table 1.
Other Adverse Reactions [see Adverse Reactions (6.1)] | Recurrent Grade 4 | Permanently discontinue ENSACOVE.
ALT = alanine aminotransferase; AST = aspartate aminotransferase; bpm = beats per minute; HR = heart rate; ULN = upper limit of normal
*Graded per National Cancer Institute Common Terminology Criteria for Adverse Events. Version 4.03.

3 DOSAGE FORMS AND STRENGTHS

ENSACOVE capsules are available as:

- 25 mg: size 2 capsule, white opaque cap and body, with “X-396” on the cap and “25 mg” on the body printed in blue ink. Each capsule contains the equivalent of 25 mg of ensartinib.

- 100 mg: size 0 capsule, blue opaque cap and yellow opaque body, with “X-396” on the cap and “100 mg” on the body printed in white ink. Each capsule contains the equivalent of 100 mg of ensartinib.

4 CONTRAINDICATIONS

ENSACOVE is contraindicated in patients who have experienced a severe hypersensitivity reaction to ENSACOVE, FD&C Yellow No. 5 (tartrazine), or to any of its components [see Warnings and Precautions (5.10)].

5 WARNINGS AND PRECAUTIONS

5.1 Interstitial Lung Disease/Pneumonitis

ENSACOVE can cause severe interstitial lung disease (ILD)/pneumonitis.

In the pooled safety population [see Adverse Reactions (6.1)], ILD/pneumonitis occurred in 5% of patients treated with ENSACOVE, including Grade 3 in 1.3% and Grade 4 in 0.4%. ILD/pneumonitis leading to dose interruption occurred in 0.4% and permanent discontinuation of ENSACOVE in 1.5% of patients.

Monitor patients for new or worsening symptoms indicative of ILD/pneumonitis (e.g., dyspnea, cough, and fever) during treatment with ENSACOVE. Immediately withhold ENSACOVE in patients with suspected ILD/pneumonitis. Permanently discontinue ENSACOVE if ILD/pneumonitis is confirmed [see Dosage and Administration (2.4)].

5.2 Hepatotoxicity

ENSACOVE can cause hepatotoxicity including drug-induced liver injury.

In the pooled safety population [see Adverse Reactions (6.1)], 59% of patients treated with ENSACOVE had increased alanine aminotransferase (ALT), including 5% Grade 3. Increased aspartate aminotransferase (AST) occurred in 58% of patients treated with ENSACOVE, including 1.8% Grade 3. Increased bilirubin occurred in 12% of patients treated with ENSACOVE, including 2.3% Grade 3 and 0.2% Grade 4. There was one case of drug-induced liver injury in ENSACOVE-treated patients.

The median time to first onset of increased ALT or AST was 5.3 weeks (range: 0.4 to 152 weeks). The dose of ENSACOVE was interrupted in 4.6% of patients for increased ALT or AST. Increased ALT or AST leading to dose reduction occurred in 2.6% and permanent discontinuation of ENSACOVE in 1.1% of patients. The dose of ENSACOVE was interrupted in 1.3% of patients for increased bilirubin. Increased bilirubin leading to dose reduction occurred in 0.7% and permanent discontinuation of ENSACOVE in 1.3% of patients.

Monitor liver function tests including ALT, AST, and total bilirubin at baseline and every 2 weeks during the first cycle of treatment with ENSACOVE, and then monthly and as clinically indicated. Withhold, reduce the dose, or permanently discontinue ENSACOVE based on the severity of the adverse reaction [see Dosage and Administration (2.4)].

5.3 Dermatologic Adverse Reactions

ENSACOVE can cause dermatologic adverse reactions, including drug reaction with eosinophilia and systemic symptoms (DRESS), rash, pruritus, and photosensitivity.

In the pooled safety population [see Adverse Reactions (6.1)], dermatologic adverse reactions occurred in 80% of patients receiving ENSACOVE, including Grade 3 in 14% of patients. Rash occurred in 72% of patients receiving ENSACOVE, including Grade 3 in 12% of patients. The median time to onset of rash was 9 days (range: 1 day to 17.3 months). Pruritus occurred in 32% of patients receiving ENSACOVE, with Grade 3 in 2.4%. There was one Grade 3 case (0.2%) of drug reaction with eosinophilia and systemic symptoms (DRESS).

The dose of ENSACOVE was interrupted in 12% of patients for dermatologic adverse reactions. Dermatologic adverse reactions leading to dose reduction occurred in 11% and permanent discontinuation of ENSACOVE in 1.5% of patients.

In the pooled safety population [see Adverse Reactions (6.1)], photosensitivity occurred in 0.9% of patients receiving ENSACOVE; all were Grade 1.

Monitor patients for dermatologic adverse reactions during treatment with ENSACOVE. If dermatologic adverse reactions occur, treat with antihistamine, topical or systemic steroids based on the severity. Advise patients to limit direct sun exposure while taking ENSACOVE and for at least 1 week after discontinuation. Withhold, reduce the dose, or permanently discontinue ENSACOVE based on the severity of the adverse reaction [see Dosage and Administration (2.4)].

5.4 Bradycardia

ENSACOVE can cause symptomatic bradycardia.

In the pooled safety population [see Adverse Reactions (6.1)], bradycardia (heart rate less than 60 beats per minute) occurred in 6% of patients treated with ENSACOVE. All bradycardia events were Grade 1 or 2. Bradycardia requiring dose reduction occurred in 0.2% and led to dose interruption in 0.4% of ENSACOVE-treated patients.

Monitor heart rate regularly during treatment with ENSACOVE. Withhold, reduce the dose, or permanently discontinue ENSACOVE based on severity [see Dosage and Administration (2.4)].

5.5 Hyperglycemia

ENSACOVE can cause hyperglycemia.

In the pooled safety population [see Adverse Reactions (6.1)], based on laboratory data, 44% of patients receiving ENSACOVE experienced increased blood glucose, including Grade 3 in 2.5%. The median time to onset of increased blood glucose was 5.9 weeks (0.4 weeks to 3.4 years).

Assess fasting serum glucose at baseline and monitor serum glucose periodically during treatment with ENSACOVE. Withhold, reduce the dose, or permanently discontinue ENSACOVE based on severity [see Dosage and Administration (2.4)].

5.6 Visual Disturbances

ENSACOVE can cause visual disturbances including blurred vision, diplopia, photopsia, vitreous floaters, visual impairment, visual field defect, and reduced visual acuity.

In the pooled safety population [see Adverse Reactions (6.1)], 8% of patients receiving ENSACOVE experienced visual disturbance, including 0.2% Grade 3. Visual disturbances led to dose interruption in 0.4% of patients.

Obtain an ophthalmologic evaluation in patients with new or worsening visual symptoms during treatment with ENSACOVE. Withhold, reduce the dose, or permanently discontinue ENSACOVE based on severity [see Dosage and Administration (2.4)].

5.7 Increased Creatine Phosphokinase

In the pooled safety population [see Adverse Reactions (6.1)], of the 203 patients with creatine phosphokinase (CPK) laboratory data available, increased CPK occurred in 43% of patients who received ENSACOVE. The incidence of Grade 3 increased CPK was 1.5% and 0.5% were Grade 4. The median time to onset of increased CPK was 123 days (range: 13 days to 22 months). Increased CPK leading to dose interruption occurred in 0.2% and dose reduction in 0.4%.

Advise patients to report any unexplained muscle pain, tenderness, or weakness. Monitor CPK levels during treatment with ENSACOVE. Withhold, reduce the dose, or permanently discontinue ENSACOVE based on severity [see Dosage and Administration (2.4), Adverse Reactions (6.1)].

5.8 Hyperuricemia

ENSACOVE can cause hyperuricemia.

In the pooled safety population [see Adverse Reactions (6.1)], based on adverse reactions, 6% of patients experienced hyperuricemia, with 0.4% Grade 3 and 0.7% Grade 4. Nine patients (1.9%) required hydration and two patients (0.4%) required urate-lowering medication.

Monitor serum uric acid levels prior to initiating ENSACOVE and periodically during treatment. Initiate treatment with urate-lowering medications as clinically indicated. Withhold, reduce the dose, or permanently discontinue ENSACOVE based on severity [see Dosage and Administration (2.4)].

5.9 Embryo-Fetal Toxicity

Based on findings from animal studies and its mechanism of action, ENSACOVE can cause fetal harm when administered to a pregnant woman. In embryo-fetal developmental studies, oral administration of ensartinib to pregnant rats during the period of organogenesis caused adverse developmental outcomes, including embryo-fetal mortality, alterations to growth, and structural abnormalities. Adverse embryo-fetal findings were seen at maternal exposures approximately equivalent to the human exposure at the recommended dose of 225 mg/day based on area under the curve (AUC). Advise pregnant women and females of reproductive potential of the potential risk to a fetus. Advise females of reproductive potential to use effective contraception during treatment with ENSACOVE and for 1 week after the last dose. Advise males with female partners of reproductive potential to use effective contraception during treatment with ENSACOVE and for 1 week after the last dose [see Use in Specific Populations (8.1, 8.3) and Clinical Pharmacology (12.1)].

5.10 FD&C Yellow No. 5 (Tartrazine)

This product contains FD&C Yellow No. 5 (tartrazine) which may cause allergic-type reactions (including bronchial asthma) in certain susceptible persons. Although the overall incidence of FD&C Yellow No. 5 (tartrazine) sensitivity in the general population is low, it is frequently seen in patients who also have aspirin hypersensitivity.

6 ADVERSE REACTIONS

The following clinically significant adverse reactions are described elsewhere in the labeling:

- Interstitial Lung Disease/Pneumonitis [see Warnings and Precautions (5.1)]
- Hepatoxicity [see Warnings and Precautions (5.2)]
- Dermatologic Adverse Reactions [see Warnings and Precautions (5.3)]
- Bradycardia [see Warnings and Precautions (5.4)]
- Hyperglycemia [see Warnings and Precautions (5.5)]
- Visual Disturbances [see Warnings and Precautions (5.6)]
- Increased Creatine Phosphokinase [see Warnings and Precautions (5.7)]
- Hyperuricemia [see Warnings and Precautions (5.8)]
- FD&C Yellow No. 5 (Tartrazine) [see Warnings and Precautions (5.10)]

6.1 Clinical Trials Experience

Because clinical trials are conducted under widely varying conditions, adverse reaction rates observed in the clinical trials of a drug cannot be directly compared to rates in the clinical trials of another drug and may not reflect the rates observed in practice.

The pooled safety population described in the WARNINGS AND PRECAUTIONS reflects exposure to ENSACOVE as a single agent in 458 patients with locally advanced or metastatic ALK-positive NSCLC in the following trials: eXALT3 Study (N=143) [see Clinical Studies (14.1)], Study 101 (NCT01625234, N=98), Study BTP-28311 (NCT02959619, N=35), and Study BTP-42322 (NCT03215693, N=182). Patients received ENSACOVE 225 mg orally once daily, with or without food, until disease progression or unacceptable toxicity. Among 458 patients who received ENSACOVE, 63% were exposed for 6 months or longer and 47% were exposed for greater than one year. In this pooled safety population, the most common adverse reactions (≥20%) were rash, musculoskeletal pain, constipation, pruritus, cough, nausea, edema, vomiting, fatigue, and pyrexia. The most frequent Grade 3 or 4 laboratory abnormalities (≥2%) were increased uric acid, decreased lymphocytes, increased alanine aminotransferase, decreased phosphate, increased gamma glutamyl transferase, increased magnesium, increased amylase, decreased sodium, increased glucose, decreased hemoglobin, increased bilirubin, decreased potassium, and increased creatine phosphokinase.

TKI-naive ALK-Positive Locally Advanced or Metastatic NSCLC

The safety of ENSACOVE was evaluated in the eXALT3 study [see Clinical Studies (14.1)]. Patients received ENSACOVE 225 mg orally once daily, with or without food, until disease progression or unacceptable toxicity. Among patients who received ENSACOVE, 78% were exposed for 6 months or longer and 66% were exposed for greater than one year.

The median age of patients who received ENSACOVE was 54 years (range: 25-86); 50% male; 54% Asian, 43% White; 0.7% Black or African American; and 11% Hispanic or Latino.

Serious adverse reactions occurred in 23% of patients treated with ENSACOVE. Serious adverse reactions that occurred in ≥1% were pneumonia (4.9%), hemorrhage (2.1%), rash (2.1%) and cellulitis (1.4%). One fatal adverse reaction (0.7%) occurred due to bronchopneumonia.

Permanent discontinuation of ENSACOVE due to an adverse reaction occurred in 12% of patients. Adverse reactions which resulted in permanent discontinuation of ENSACOVE (≥1%) included increased blood bilirubin (1.4%), increased conjugated bilirubin (1.4%), increased ALT (2.1%), increased AST (2.1%), and pneumonitis/ILD (2.1%).

Dose interruptions of ENSACOVE due to an adverse reaction occurred in 41% of patients. Adverse reactions which required dose interruptions (≥2%) included rash (13%), increased ALT (6%), edema (2.8%), pruritus (2.8%), pyrexia (2.8%), pneumonia (3.5%), increased AST (2.1%), hemorrhage (2.1%), and decreased appetite (2.1%).

Dose reductions of ENSACOVE due to an adverse reaction occurred in 24% of patients. Adverse reactions which required dose reductions (≥2%) included rash (11%), increased ALT (4.2%), pruritus (2.8%), and edema (2.1%).

Tables 3 and 4 summarize the most frequent adverse reactions and laboratory abnormalities, respectively.

Table 3: Adverse Reactions (≥10%) in Patients with ALK-Positive Locally Advanced or Metastatic NSCLC Who Received ENSACOVE in eXALT3 Study
 |  | ENSACOVE N = 143 |  | Crizotinib N = 146
Adverse Reaction |  | All Grades % | Grade 3 or 4 % | All Grades; % | Grade 3 or 4; %
Skin and Subcutaneous Tissue Disorders
Rasha |  | 66 | 12 | 10 | 0
Pruritusb |  | 30 | 2.1 | 4.1 | 0
Alopecia |  | 11 | 0 | 4.8 | 0
Dry Skin |  | 10 | 0.7 | 0.7 | 0
Musculoskeletal and Connective Tissue Disorders
Musculoskeletal Painc |  | 36 | 1.4 | 20 | 0
Respiratory, Thoracic and Mediastinal Disorders
Coughd |  | 31 | 0.7 | 16 | 0
Gastrointestinal Disorders
Constipation |  | 31 | 0 | 26 | 0
Nausea |  | 28 | 1.4 | 30 | 2.1
Vomitinge |  | 16 | 0.7 | 32 | 0
General Disorders and Administration Site Conditions
Edemaf |  | 27 | 2.1 | 28 | 2.1
Pyrexiag |  | 22 | 0.7 | 10 | 0.7
Fatigueh |  | 21 | 0.7 | 14 | 1.4
Metabolism and Nutrition Disorders
Decreased appetite |  | 15 | 0 | 12 | 1.4
Infection and Infestation
Respiratory Tract Infection |  | 13 | 0.7 | 10 | 0
Nervous System Disorders
Dizzinessi |  | 12 | 0.7 | 14 | 0.7
Dysgeusia |  | 10 | 0 | 11 | 0
Vascular Disorders
Hemorrhagej |  | 10 | 1.4 | 4.8 | 0
Adverse reactions were graded using NCI CTCAE version 4.03.
a Includes dermatitis, dermatitis acneiform, dermatitis bullous, drug eruption, eczema, exfoliative rash, palmar-plantar erythrodysaesthesia, rash, rash erythematous, rash generalized, rash macular, rash maculo-papular, rash morbilliform, rash papular, rash pruritic, rash pustular, skin exfoliation, and vulvovaginal rash
b Includes ear pruritus, eye pruritus, eyelids pruritus, lip pruritus, pruritus, and pruritus generalized
c Includes arthritis, spinal pain, myalgia, musculoskeletal pain, back pain, pain in extremity, neck pain, arthralgia, non-cardiac chest pain, bone pain, musculoskeletal chest pain, musculoskeletal discomfort
d Includes cough, productive cough, upper-airway cough syndrome
e Includes vomiting and retching
f Includes eyelid edema, face edema, generalized edema, localized edema, edema, edema peripheral, gravitational edema, skin edema, eye edema, and periorbital edema
g Includes pyrexia and hyperthermia
h Includes fatigue and asthenia
i Includes dizziness, vertigo, postural dizziness
j Includes hemoptysis, intracranial hemorrhage, gastrointestinal hemorrhage, hematuria, upper gastrointestinal hemorrhage, vaginal hemorrhage, gingival bleeding, vitreous hemorrhage, epistaxis, rectal hemorrhage, anal hemorrhage

Table 4: Select Laboratory Abnormalities (≥20%) That Worsened from Baseline in Patients with ALK-Positive Locally Advanced or Metastatic NSCLC Who Received ENSACOVE in eXALT3 Study
 | ENSACOVE N = 143 |  | Crizotinib N = 146
Lab Abnormality | All Grades % | Grade 3 or 4 % | All Grades % | Grade 3 or 4 %
Chemistry
Alanine aminotransferase increased | 73 | 5 | 74 | 8
Alkaline phosphatase increased | 64 | 2.2 | 50 | 0.7
Aspartate aminotransferase increased | 64 | 1.4 | 62 | 3.5
Glucose increased | 49 | 5 | 35 | 0.7
Albumin decreased | 46 | 0.7 | 56 | 1.4
Phosphate decreased | 39 | 7 | 42 | 4.9
Urate increased | 39 | 39 | 27 | 27
Creatinine increased | 37 | 0 | 27 | 0
Calcium decreased | 36 | 1.4 | 64 | 4.9
Sodium decreased | 27 | 4.3 | 27 | 4.2
Hematology
Lymphocytes decreased | 57 | 7 | 47 | 5
Hemoglobin decreased | 43 | 0.7 | 31 | 1.4
Adverse reactions were graded using NCI CTCAE version 4.03.
ALT = Alanine aminotransferase; AST = Aspartate aminotransferase

Clinically relevant adverse reactions in <10% of patients who received ENSACOVE included interstitial lung disease, photosensitivity, increased creatinine phosphokinase, bradycardia, and visual disturbances.

7 DRUG INTERACTIONS

7.1 Effect of Other Drugs on ENSACOVE

Table 5 describes drug interactions where concomitant use of another drug affects ENSACOVE.

Table 5: Effect of Other Drugs on ENSACOVE
Strong or Moderate CYP3A Inhibitors
Prevention or Management | Avoid concomitant use of strong or moderate CYP3A inhibitors with ENSACOVE.
Mechanism and Clinical Effect(s) | This recommendation is based upon a mechanistic understanding of ensartinib pharmacokinetics and it being a CYP3A4 substrate in vitro [see Clinical Pharmacology (12.3)]. Concomitant use with strong or moderate CYP3A inhibitors may increase ensartinib exposure; however, this has not been studied clinically.
Strong or Moderate CYP3A Inducers
Prevention or Management | Avoid concomitant use of strong or moderate CYP3A inducers with ENSACOVE.
Mechanism and Clinical Effect(s) | This recommendation is based upon a mechanistic understanding of ensartinib pharmacokinetics and it being a CYP3A4 substrate in vitro [see Clinical Pharmacology (12.3)]. Concomitant use with strong or moderate CYP3A inducers may decrease ensartinib exposure; however, this has not been studied clinically.
P-gp Inhibitors
Prevention or Management | Avoid concomitant use of P-gp inhibitors with ENSACOVE.
Mechanism and Clinical Effect(s) | This recommendation is based upon a mechanistic understanding of ensartinib pharmacokinetics and it being a P-gp substrate in vitro [see Clinical Pharmacology (12.3)]. Concomitant use with P-gp inhibitors may increase ensartinib exposure; however, this has not been studied clinically.

8 USE IN SPECIFIC POPULATIONS

8.1 Pregnancy

Risk Summary

Based on findings from animal studies and its mechanism of action [see Clinical Pharmacology (12.1)], ENSACOVE can cause fetal harm when administered to a pregnant woman. There are no available data on the use of ENSACOVE in pregnant women to inform a drug-associated risk. Oral administration of ensartinib to pregnant rats during the period of organogenesis caused adverse developmental outcomes, including embryo-fetal mortality, alterations to growth, and structural abnormalities. Adverse embryo-fetal findings were seen at maternal exposures approximately equivalent to the human exposure at the recommended dose of 225 mg/day based on AUC (see Data). Advise pregnant women of the potential risk to a fetus.

In the U.S. general population, the estimated background risk of major birth defects and miscarriage in clinically recognized pregnancies is 2% to 4% and 15% to 20%, respectively.

Data

Animal Data

In an embryo-fetal development study, pregnant rats received 20, 40, or 80 mg/kg/day of ensartinib during the period of organogenesis (gestation day 6 to 17). Ensartinib doses ≥40 mg/kg/day (approximately equivalent to the human exposure at the recommended dose of 225 mg/day based on AUC) resulted in an increase in the incidence of fetal malformations (aortic dislocation, ventricular septal defect, separated vertebrae) and dose-dependent delayed skeletal development, including decreased or delayed ossification of the vertebrae. Ensartinib at 80 mg/kg (approximately 6.4 times the human exposure at the recommended dose of 225 mg/day based on AUC) resulted in maternal toxicity (reduced body weight and food consumption), decreased fetal body weight, increased pre- and post-implantation loss, decreases in the number of live fetuses, and visceral variations (missing renal papillae, pyelectasis).

8.2 Lactation

Risk Summary

There are no data on the presence of ensartinib or its metabolites in human milk, the effects on the breastfed child, or the effects on milk production. Because of the potential for serious adverse reactions in breastfed children, advise women not to breastfeed during treatment with ENSACOVE and for 1 week after the last dose.

8.3 Females and Males of Reproductive Potential

ENSACOVE can cause fetal harm when administered to a pregnant woman [see Use in Specific Populations (8.1)].

Pregnancy Testing

Verify the pregnancy status of females of reproductive potential prior to initiating ENSACOVE.

Contraception

Females

Advise females of reproductive potential to use effective contraception during treatment with ENSACOVE and for at 1 week after the last dose.

Males

Advise male patients with female partners of reproductive potential to use effective contraception during treatment with ENSACOVE and for 1 week after the last dose.

8.4 Pediatric Use

The safety and effectiveness of ENSACOVE in pediatric patients have not been established.

8.5 Geriatric Use

Of the 458 patients enrolled in clinical studies and received ENSACOVE 225 mg once daily, 16% of the participants were aged 65 years or older. Clinical studies of ENSACOVE did not include sufficient numbers of patients ages 65 and over to determine whether they respond differently from younger patients. Exploratory analysis suggests a higher incidence of serious adverse events (43% vs 27%), more frequent adverse events leading to treatment discontinuations (18% vs 10%) and dose modifications (34% vs 16%) in patients 65 years or older as compared to those younger than 65 years.

8.6 Hepatic Impairment

Ensartinib is primarily metabolized by the liver and patients with hepatic impairment may have increased exposures [see Clinical Pharmacology (12.3)]. Avoid use of ENSACOVE for patients with severe hepatic impairment (total bilirubin >3 times ULN and any AST) since it has not been studied in this population. Monitor patients with moderate hepatic impairment (total bilirubin >1.5 to ≤ 3 ULN and any AST) for increased adverse reactions and adjust ENSACOVE dosage as clinically indicated [see Dosage and Administration (2.4), Warnings and Precautions (5.2)]. No dosage modification is recommended for patients with mild hepatic impairment (total bilirubin ≤ upper limit of normal (ULN) and AST > ULN or total bilirubin 1 to 1.5 x ULN and any AST).

11 DESCRIPTION

ENSACOVE capsules contain ensartinib, a kinase inhibitor, present as ensartinib hydrochloride with the chemical name 6-amino-5-[(1R)-1-(2,6-dichloro-3-fluorophenyl)ethoxy]-N-{4-[(3R,5S)- 3,5-dimethylpiperazine-1-carbonyl]phenyl}pyridazine-3-carboxamide, dihydrochloride. The molecular formula is C26H27Cl2FN6O3·2HCl and its molecular weight is 634.4 g/mol with the following structure:

ENSACOVE capsules are intended for oral administration and are available in two dosage strengths: 25 mg ensartinib (equivalent to 28.25 mg ensartinib hydrochloride) and 100 mg ensartinib (equivalent to 113.02 mg ensartinib hydrochloride).

The inactive ingredients of ENSACOVE capsules are microcrystalline cellulose and stearic acid. The inactive ingredients of the 25 mg empty capsule shells are hypromellose and titanium dioxide. The inactive ingredients of the 100 mg empty capsules shells are black iron oxide, FD&C Blue No. 1, FD&C Yellow No. 5, hypromellose, red iron oxide, and titanium dioxide.

The imprinting ink for the 25 mg capsules contains butyl alcohol, dehydrated alcohol, FD&C Blue No. 2, isopropyl alcohol, propylene glycol, shellac, and strong ammonia solution. The imprinting ink for the 100 mg capsules contains butyl alcohol, dehydrated alcohol, isopropyl alcohol, povidone, propylene glycol, shellac, sodium hydroxide, and titanium dioxide.

12 CLINICAL PHARMACOLOGY

12.1 Mechanism of Action

Ensartinib is a kinase inhibitor of anaplastic lymphoma kinase (ALK) and inhibits other kinases including MET and ROS1. In vitro, ensartinib inhibited phosphorylation of ALK and its downstream signaling proteins AKT, ERK, and S6, thereby blocking ALK-mediated signaling pathways and inhibiting proliferation in cell lines harboring ALK fusions and mutations. In vivo, ensartinib showed anti-tumor activity in a mouse xenograft model of human NSCLC harboring an ALK fusion.

12.2 Pharmacodynamics

Exposure-response relationship

Ensartinib exposure-response relationships and the time course of the pharmacodynamic response have not been fully characterized.

Cardiac Electrophysiology

At the approved recommended dosage, a mean increase in the QTc interval > 20 ms was not observed.

12.3 Pharmacokinetics

Ensartinib mean (coefficient of variation [CV%]) maximum concentration (Cmax) is 292 ng/mL (60%), and the area under the concentration-time curve (AUC0–24h) is 4,920 ng·h /ml (62%) at the approved recommended dosage. Ensartinib steady state is reached within 15 days with a mean accumulation ratio of 2.7.

Absorption

Ensartinib median (minimum, maximum) time to reach Cmax (Tmax) at steady state is 3 hours (2, 8 hours).

Effect of Food

No clinically significant differences in ensartinib pharmacokinetics were observed following administration of ENSACOVE with a high-fat meal (total 800-1000 calories, > 50% fat) compared to fasted conditions.

Distribution

Ensartinib mean (CV%) apparent volume of distribution is 1,720 L (42%). Ensartinib is 91.6% bound to human plasma protein.

Elimination

Ensartinib mean (standard deviation [SD]) steady-state half-life (t1/2) is 30 (20) hours.

Metabolism

Ensartinib is predominantly metabolized by CYP3A.

Excretion

Following a single oral 200 mg dose of radiolabeled ensartinib, 91% of the radioactivity was recovered in feces (38% as unchanged) and 10% in urine (4.4% as unchanged).

Specific Populations

No clinically significant differences in the pharmacokinetics of ensartinib were observed based on age (20 to 86 years), sex, race (Asian vs White), body weight (38 to 148 kg), mild to moderate renal impairment (eGFR 30 to 89 mL/min) and mild hepatic impairment (total bilirubin ≤ upper limit of normal (ULN) and AST > ULN or total bilirubin 1 to 1.5 x ULN and any AST).

The effect of severe renal impairment (eGFR 15 to 29 mL/min), end-stage renal disease (eGFR <15 mL/min) with or without hemodialysis, and moderate (total bilirubin >1.5 to ≤ 3 ULN and any AST) or severe (total bilirubin >3 times ULN and any AST) hepatic impairment on ensartinib pharmacokinetics is unknown.

Drug Interaction Studies

In Vitro Studies

Cytochrome P450 (CYP) Enzymes: Ensartinib does not inhibit CYP1A2, CYP2B6, CYP2C8, CYP2C9, CYP2C19, CYP2D6 and does not induce CYP1A2, CYP2B6, or CYP3A.

Transporter Systems: Ensartinib is a P-gp substrate but is not a substrate of BCRP, OATP1B1, OATP1B3, OAT1, OAT3, OCT1 or OCT2.

Ensartinib does not inhibit BCRP, P-gp, OATP1B1, OATP1B3, OAT1, OAT3, OCT1, OCT2 or OCT3.

13 NONCLINICAL TOXICOLOGY

13.1 Carcinogenesis, Mutagenesis, Impairment of Fertility

Carcinogenicity studies have not been conducted with ensartinib.

Ensartinib was not mutagenic in a bacterial reverse mutation (Ames) assay and was not clastogenic in an in vitro human lymphocyte chromosome aberration assay or an in vivo rat bone marrow micronucleus assay.

Dedicated fertility studies were not conducted with ensartinib. No adverse effects on male or female reproductive organs were observed in up to 3-month repeat-dose toxicology studies conducted in rats and dogs.

14 CLINICAL STUDIES

14.1 TKI-naive ALK-Positive Locally Advanced or Metastatic NSCLC (eXALT3 Study)

The efficacy of ENSACOVE was evaluated in eXALT3 (NCT02767804), an open-label, randomized, active-controlled, multicenter study in adult patients with locally advanced (stage IIIB following prior chemotherapy or chemoradiation or not amenable to curative intent therapy) or metastatic ALK-positive NSCLC. Patients were required to have ALK-positive NSCLC in tumor specimens as determined in local laboratories using immunohistochemistry (IHC), next-generation sequencing (NGS), polymerase chain reaction (PCR) or fluorescence in situ hybridization (FISH) tests. Of these patients, 85% (247/290) had centrally confirmed ALK rearrangements with the Vysis Break Apart FISH Probe Kit. Patients could have received one prior regimen of chemotherapy but could not have previously received an ALK-targeted therapy; patients with an ECOG performance status of 0, 1, or 2 were eligible. Patients with asymptomatic, untreated brain metastases who were not on corticosteroids and patients with asymptomatic, treated brain metastases who were on stable or decreasing dose of corticosteroids were eligible. Patients were required to have completed radiation therapy at least 2 weeks, or chemotherapy at least 4 weeks, prior to enrollment. Patients with leptomeningeal disease were ineligible.

Patients were randomized 1:1 to receive ENSACOVE 225 mg orally once daily or crizotinib 250 mg orally twice daily in 28-day cycles until disease progression or unacceptable toxicity. Randomization was stratified by prior chemotherapy (0 vs. 1), ECOG performance status (0 or 1 vs. 2), presence of central nervous system (CNS) metastases (yes or no), and geographic region (Asia vs. the rest of the world). Tumor assessments were performed every 8 weeks.

The main efficacy outcome measure was progression-free survival (PFS) as evaluated by Blinded Independent Central Review (BICR) according to RECIST version 1.1. The key secondary efficacy outcome measure was overall survival (OS); other secondary outcome measures included CNS response rate, time to CNS progression, and overall response rate (ORR).

A total of 290 patients were randomized to ENSACOVE (n=143) or crizotinib (n=147). The baseline demographic characteristics of the overall study population were median age 54 years (range: 25-90); 16% age > 65 years; 51% male; 56% Asian; 41% White and 1% Black; 7% Hispanic or Latino; ECOG PS 0 or 1 (95%); and 62% never smokers. Patients had Stage IIIB (8%) or Stage IV NSCLC (92%); 32% had received prior chemotherapy and 17% had received prior radiation. Baseline CNS metastases were present in 36% of the patients.

The eXALT3 study demonstrated a statistically significant improvement in PFS for patients randomized to ENSACOVE compared to patients randomized to crizotinib. The efficacy results as assessed by BICR are summarized in Table 6 and Figure 1.

Table 6: Efficacy Results for eXALT3 Study According to BICR Assessment
Efficacy Parameter | ENSACOVE N=143 | Crizotinib N=147
Progression-free survival
Number of events, n (%) | 59 (41%) | 80 (54%)
Progressive disease, n (%) | 51 (36%) | 77 (52%)
Death, n (%) | 8 (6%) | 3 (2%)
Median, months (95% CI) | 25.8 (21.8, NE) | 12.7 (9.2, 16.6)
Hazard ratio (95% CI) | 0.56 (0.40, 0.79)
p-valuea | 0.0008
Overall response rate
Overall response rate % (95% CI) | 74% (66, 81) | 67% (58, 74)
Complete response % | 12% | 5%
Partial response % | 62% | 61%
Duration of response
Number of responders, n | 106 | 98
Median, months (95% CI) | NE (22.0, NE) | 27.3 (12.9, NE)
CI = Confidence Interval, NE=not estimable, BICR = Blinded Independent Central Review
a p-value based on unstratified log-rank test

Figure 1 Kaplan-Meier Plot of Progression-Free Survival by IRR from Study 301 (eXALT3)

At the time of the primary PFS analysis, OS results were immature. At the time of final analysis of OS, there was no statistically significant difference (p-value = 0.4570) between ENSACOVE and crizotinib. Median OS was 63.2 months in the ENSACOVE arm and 55.7 months in the crizotinib arm, with the hazard ratio of 0.88 (95% CI: 0.63, 1.23).

The results of the pre-specified analyses of CNS response rate by BICR in patients with baseline measurable CNS disease are summarized in Table 7.

Table 7: IRR-assessed CNS Responses in Patients with Measurable CNS Disease at Baseline in Study 301 (eXALT3)
Efficacy Parameter | ENSACOVE N=17 | crizotinib N=24
CNS overall response rate % (95% CI) | 59% (33, 82) | 21% (7, 42)
Complete response % | 24% | 8%
Partial response % | 35% | 13%
Duration of Response
Number of responders, n | 10 | 5
Patients with DOR ≥ 12 months | 30% | 40%
BICR = Blinded Independent Central Review; CI = Confidence Interval

16 HOW SUPPLIED

ENSACOVE (ensartinib) capsules are supplied as follows:

Capsule Strength | Description | Package Configuration | NDC Code
25 mg | Size 2 capsule, white opaque cap and body, with “X-396” on the cap and “25 mg” on the body printed in blue ink. | Bottles of 30 | 83076-1025-3
100 mg | Size 0 capsule, blue opaque cap and yellow opaque body, with “X- 396” on the cap and “100 mg” on the body printed in white ink. | Bottles of 60 | 83076-1100-6

Store at controlled room temperature 20ºC to 25ºC (68ºF to 77ºF); excursions permitted to 15ºC to 30ºC (59ºF to 86ºF) [see USP Controlled Room Temperature]. Store and dispense in the original bottle with desiccant to protect from moisture. Do not remove desiccant from bottle. Keep out of reach of children

17 PATIENT COUNSELING INFORMATION

Advise the patient to read the FDA-approved patient labeling (Patient Information).

Interstitial Lung Disease (ILD)/Pneumonitis

Inform patients of the risk of severe ILD/pneumonitis during treatment with ENSACOVE. Advise patients to contact their healthcare provider immediately to report new or worsening respiratory symptoms [see Warnings and Precautions (5.1)].

Hepatoxicity

Inform patients of the potential risk of hepatoxicity during treatment with ENSACOVE and of the need to monitor for aspartate aminotransferase (AST), alanine aminotransferase (ALT) and total bilirubin elevations during treatment with ENSACOVE. Advise patients to inform their healthcare provider of any new or worsening symptoms [see Warnings and Precautions (5.2)].

Dermatologic Adverse Reactions

Inform patients of the potential risk of dermatologic adverse reactions, including rash, pruritus, and photosensitivity during treatment with ENSACOVE. If dermatologic reactions occur, advise patients to limit sun exposure while taking ENSACOVE and for at least 1 week after the final dose [see Warnings and Precautions (5.3)].

Bradycardia

Advise patients of the risk of bradycardia during treatment with ENSACOVE and to report any symptoms of bradycardia. Advise patients to inform their healthcare provider about the use of any heart or blood pressure medications during treatment with ENSACOVE [see Warnings and Precautions (5.4)].

Hyperglycemia

Inform patients of the risks of new or worsening hyperglycemia during treatment with ENSACOVE and the need to periodically monitor glucose levels. Advise patients with diabetes mellitus or glucose intolerance that antihyperglycemic medications may need to be adjusted during treatment with ENSACOVE [see Warnings and Precautions (5.5)].

Visual Disturbances

Advise patients to inform their healthcare provider of any new or worsening vision symptoms during treatment with ENSACOVE [see Warnings and Precautions (5.6)].

Creatine Phosphokinase (CPK) Elevation

Inform patients of the signs and symptoms of creatine phosphokinase (CPK) elevation and the need for monitoring during treatment with ENSACOVE. Advise patients to inform their healthcare provider of any new or worsening symptoms [see Warnings and Precautions (5.7)].

Hyperuricemia

Inform patients of the signs and symptoms of hyperuricemia. Advise patients to inform their healthcare provider if they experience signs or symptoms associated with hyperuricemia during treatment with ENSACOVE [see Warnings and Precautions (5.8)].

Embryo-Fetal Toxicity

Advise females of reproductive potential of the potential risk to a fetus. Advise females to inform their healthcare provider of a known or suspected pregnancy. Advise females of reproductive potential to use effective contraception during treatment with ENSACOVE and for 1 week after the last dose [see Warnings and Precautions (5.9) and Use in Specific Populations (8.1,8.3)].

Advise males with female partners of reproductive potential to use effective contraception during treatment with ENSACOVE and for 1 week after the last dose [see Warnings and Precautions (5.9) and Use in Specific Populations (8.3)].

FD&C Yellow No. 5 (tartrazine)

Advise patients that this product contains FD&C Yellow No. 5 (tartrazine) which may cause allergic-type or asthma-type reactions in certain susceptible persons (e.g., patients who also have aspirin hypersensitivity) [see Warnings and Precautions (5.10)]. Advise patients to contact their healthcare provider and seek medical help right away if they develop symptoms of an allergic reaction to FD&C Yellow No. 5 (tartrazine).

Lactation

Advise women not to breastfeed during treatment with ENSACOVE and for 1 week after the last dose [see Use in Specific Populations (8.2)].

Administration

Instruct patients to take ENSACOVE once a day with or without food and to swallow ENSACOVE capsules whole [see Dosage and Administration (2.2)].

Missed Dose

Advise patients to take ENSACOVE at the same time each day. If a dose is missed, then they should take the missed dose as soon as possible unless the next dose is due within 12 hours. Patients should be instructed not to take 2 doses at the same time to make up for a missed dose. In addition, instruct patients not to take an extra dose if they vomit after taking ENSACOVE [see Dosage and Administration (2.2)].

Manufactured for: Xcovery Holdings, Inc. Miami, FL 33131

ENSACOVE is a trademark of Xcovery Holdings, Inc.

©2026, Xcovery Holdings, Inc. All rights reserved.

PATIENT INFORMATION
ENSACOVETM (En-sa-kowv)
(ensartinib)
capsules, for oral use

What is ENSACOVE?

ENSACOVE is a prescription medicine used to treat adults with non-small cell lung cancer (NSCLC):

- that is caused by an abnormal anaplastic lymphoma kinase (ALK) gene,
- that has spread to other parts of your body, and
- who have not received medicines called ALK-inhibitors.

Your healthcare provider will perform a test to make sure that ENSACOVE is right for you.

It is not known if ENSACOVE is safe and effective in children.

Do not use ENSACOVE if you are allergic to ENSACOVE, FD&C No. 5 (tartrazine), or to any of the ingredients in ENSACOVE. See the end of this leaflet for a complete list of ingredients in ENSACOVE.

Before using ENSACOVE, tell your healthcare provider about all of your medical conditions, including if you:

- have lung or breathing problems
- have liver problems
- have problems with your heartbeat
- have diabetes mellitus or glucose intolerance
- have problems with your vision
- are pregnant or plan to become pregnant. ENSACOVE can harm your unborn baby.
  - Your healthcare provider will do a pregnancy test before you start treatment with ENSACOVE.
  - Tell your healthcare provider right away if you become pregnant or think you may be pregnant during treatment with ENSACOVE.
    - Females who are able to become pregnant should use effective birth control (contraception) during treatment with ENSACOVE and for 1 week after the last dose of ENSACOVE. Talk to your healthcare provider about birth control choices that are right for you during treatment with ENSACOVE.
    - Males who who have female partners who are able to become pregnant should use effective birth control (contraception) during treatment with ENSACOVE and for 1 week after the last dose of ENSACOVE.
- are breastfeeding or plan to breastfeed. It is not known if ENSACOVE passes into your breast milk. Do not breastfeed during treatment with ENSACOVE and for 1 week after the last dose. Talk to your healthcare provider about the best way to feed your baby during this time.

Tell your healthcare provider about all the other medicines you take, including prescription and over-the-counter medicines, vitamins and herbal supplements.

Certain other medicines may affect the way that ENSACOVE works and may increase your risk of certain side effects.

Know the medicines you take. Keep a list of them to show to your healthcare provider and pharmacist when you get a new medicine.

How should I take ENSACOVE?

- Take ENSACOVE exactly as your healthcare provider tells you to take it. Do not change your dose or stop taking ENSACOVE unless your healthcare provider tells you to.
- Swallow ENSACOVE capsules whole. Do not crush or chew capsules. Do not open or dissolve the contents of the capsule.
- Take ENSACOVE 1 time a day, at the same time each day.
- You may take ENSACOVE with or without food.
- If you miss a dose, take it as soon as you remember. If your next dose is due within 12 hours, skip the missed dose and take your next dose at your regular time. Do not take 2 doses of ENSACOVE on the same day to make up for the missed dose.
- If you vomit after taking a dose of ENSACOVE, do not take an extra dose. Take your next dose at your regular time.

What should I avoid while taking ENSACOVE?

- Limit your time in the sun during treatment with ENSACOVE and for at least 1 week after your last dose. ENSACOVE may make your skin sensitive to sunlight. You may burn more easily and get severe sunburns. When you are in the sun, wear a hat and protective clothing, and use a broad-spectrum sunscreen and lip balm with a Sun Protection Factor (SPF) of 30 or greater to protect against sunburn.

What are the possible side effects of ENSACOVE?

ENSACOVE can cause serious side effects, including:

- Lung problems. ENSACOVE can cause severe or life-threatening swelling (inflammation) of the lungs. Symptoms may be similar to those from lung cancer. Tell your healthcare provider right away if you get any new or worsening symptoms of lung problems during treatment with ENSACOVE, including:

- trouble breathing or shortness or breath
- chest pain

- cough with or without mucus
- fever

- Liver problems. ENSACOVE can increase enzymes called aspartate aminotransferase (AST) and alanine aminotransferase (ALT), and levels of bilirubin in your blood. Tell your healthcare provider if you get new or worsening signs or symptoms of liver problems, including:

- yellowing of your skin or the white part of your eyes
- dark or brown (tea color) urine
- nausea or vomiting
- pain on the right side of your stomach area

- bleed or bruise more easily than normal
- itchy skin
- decreased appetite
- feeling tired

- Skin reactions. ENSACOVE may cause skin reactions that require treatment. Tell your healthcare provider if you get symptoms of skin reactions, such as rash, itching, or skin swelling

- Slow heart rate (bradycardia). ENSACOVE can cause very slow heartbeats that can be severe. Your healthcare provider will check your heart rate during treatment with ENSACOVE. Tell your healthcare provider right away if you feel dizzy, lightheaded, or faint during treatment with ENSACOVE. Tell your healthcare provider if you take any heart or blood pressure medicines.

- High blood sugar (hyperglycemia). ENSACOVE can increase your blood sugar levels. Hyperglycemia is common with ENSACOVE treatment but can be serious. If you take medicine for diabetes or glucose intolerance your healthcare provider may change your medicine during treatment with ENSACOVE. Tell your healthcare provider if you get new or worsening signs and symptoms of hyperglycemia, including:

- feeling very thirsty
- needing to urinate more than usual
- feeling very hungry

- feeling sick to your stomach
- feeling weak or tired
- feeling confused

- Vision problems. ENSACOVE may cause vision problems. Your healthcare provider may refer you to an eye specialist if you develop new or worsening vision problems during treatment with ENSACOVE. Tell your healthcare provider if you have any loss of vision or any change in vision, including

- blurry vision
- double vision
- seeing flashes of light

- light hurting eyes
- new or increased floaters

- Muscle pain, tenderness, and weakness (myalgia). ENSACOVE can increase the level of an enzyme in your blood called creatine phosphokinase (CPK), which may be a sign of muscle damage. Myalgia is common with ENSACOVE treatment but can be serious. Tell your healthcare provider if you get new or worsening signs and symptoms of muscle problems, including unexplained muscle pain or muscle pain that does not go away, tenderness, or weakness.

- Increased uric acid level in your blood (hyperuricemia). ENSACOVE can cause too much uric acid in your blood. Hyperuricemia is common with ENSACOVE treatment but can be serious. Your healthcare provider may prescribe medicines if you have high blood uric acid levels. Tell your healthcare provider if you develop any of the following symptoms of hyperuricemia:

- red, hot, tender, or swollen joints, especially your big toe
- pain in your stomach-area or sides

- nausea or vomiting
- pink or brown urine

- Allergic reactions to FD&C Yellow No. 5 (tartrazine). ENSACOVE 100 mg capsules contain FD&C Yellow No. 5. FD&C Yellow No. 5 (tartrazine) that can cause allergic reactions in certain people, especially people who also have an allergy to aspirin. Tell your healthcare provider if you get hives, rash, or trouble breathing during treatment with ENSACOVE.

Your healthcare provider will do certain blood tests before and during treatment with ENSACOVE to check you for side effects.

If you have serious side effects during treatment with ENSACOVE, your healthcare provider may change your dose, stop your treatment for a period of time (temporary), or completely stop treatment with ENSACOVE.

The most common side effects of ENSACOVE are:

- rash
- muscle or bone pain
- constipation
- itching
- coughing
- nausea
- skin swelling (edema)
- vomiting

- tiredness
- fever
- increased levels of liver and pancreatic enzymes
- decreased white blood cell counts
- changes in blood levels of phosphate, magnesium, sodium, and potassium
- decreased protein (hemoglobin) in red blood cells
- increased bilirubin blood levels

These are not all the possible side effects with ENSACOVE.
Call your doctor for medical advice about side effects. You may report side effects to FDA at 1-800-FDA-1088.

How should I store ENSACOVE?

- Store ENSACOVE at room temperature between 68ºF to 77ºF (20ºC to 25ºC).
- Keep ENSACOVE capsules in the original bottle.
- The bottle of ENSACOVE capsules contains a drying agent (desiccant) to help keep your medicine dry. Do not remove the desiccant from the bottle after opening. Do not open or eat the desiccant.

Keep ENSACOVE and all medicines out of the reach of children.

General information about the safe and effective use of ENSACOVE.
Medicines are sometimes prescribed for purposes other than those listed in a Patient Information leaflet. Do not use ENSACOVE for a condition for which it was not prescribed. Do not give ENSACOVE to other people, even if they have the same symptoms you have. It may harm them. You can ask your pharmacist or healthcare provider for information about ENSACOVE that is written for health professionals.

What are the ingredients in ENSACOVE?

Active ingredient: ensartinib hydrochloride

Inactive ingredients: butyl alcohol, dehydrated alcohol, hypromellose, isopropyl alcohol, microcrystalline cellulose, propylene glycol, shellac, stearic acid, and titanium dioxide. The 25 mg capsules also contain the following inactive ingredients: FD&C Blue No. 2 and strong ammonia solution. The 100 mg capsules also contain the following inactive ingredients: black iron oxide, FD&C Blue No. 1, FD&C Yellow No. 5, povidone, red iron oxide, and sodium hydroxide.

Manufactured for: Xcovery Holdings, Inc., Miami, FL, 33131
ENSACOVE is a trademark of Xcovery Holdings, Inc.
©2024, Xcovery Holdings, Inc. All rights reserved.

For more information, call Xcovery Holdings, Inc. at (866) 367-2268.

This Patient Information has been approved by the U.S. Food and Drug Administration

Issued: 12/2024

PRINCIPAL DISPLAY PANEL - 25 mg

ENSACOVE™ (ensartinib) capsules - 25 mg

Bottle of 30 Capsules

NDC 83076-1025-3

PRINCIPAL DISPLAY PANEL - 100 mg

ENSACOVE™ (ensartinib) capsules - 100 mg

Bottle of 60 Capsules

NDC 83076-1100-6